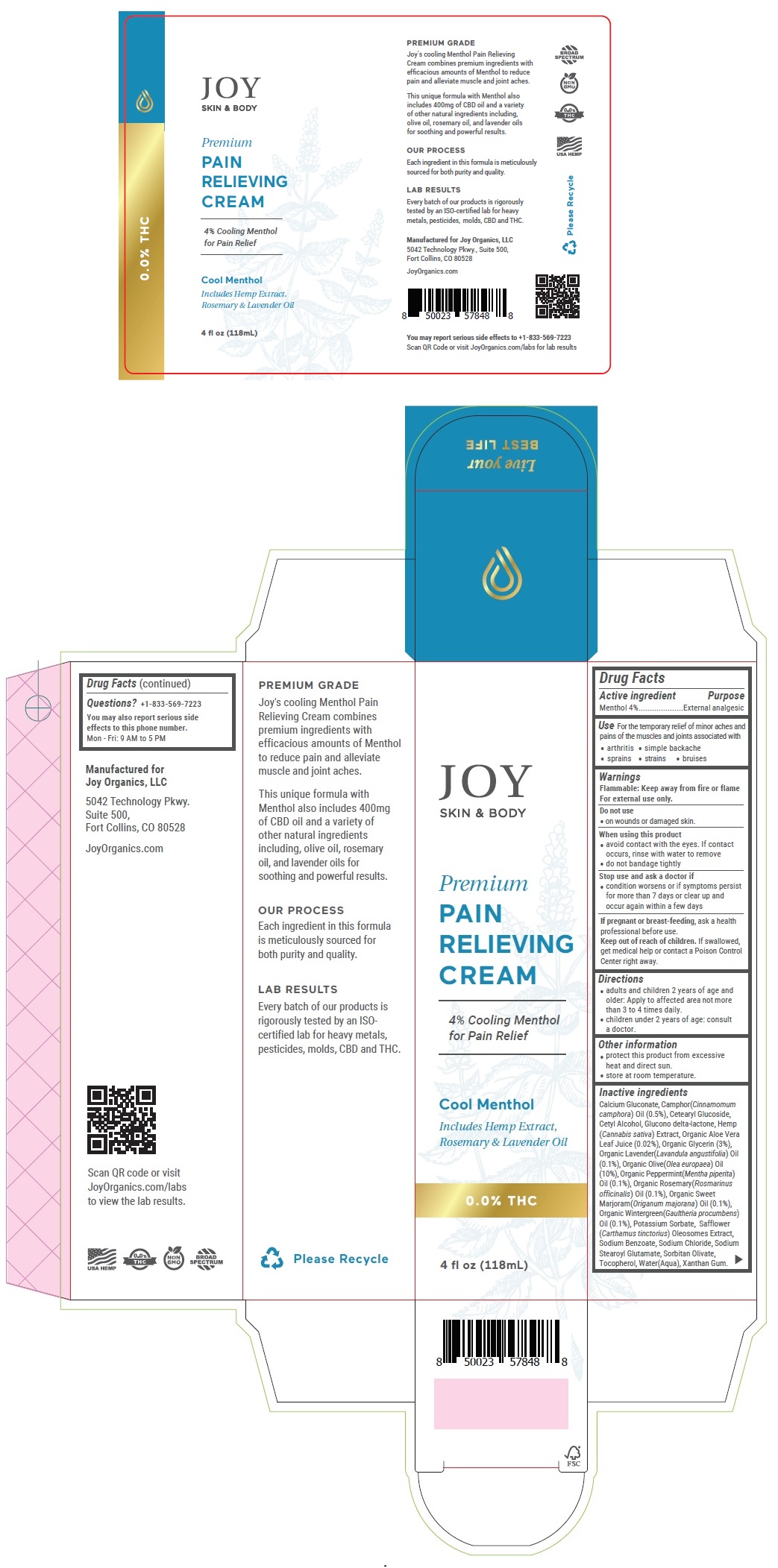 DRUG LABEL: JOY SKIN AND BODY Premium PAIN RELIEVING
NDC: 80977-101 | Form: CREAM
Manufacturer: Joy Organics Llc
Category: otc | Type: HUMAN OTC DRUG LABEL
Date: 20210310

ACTIVE INGREDIENTS: MENTHOL, UNSPECIFIED FORM 4 g/100 mL
INACTIVE INGREDIENTS: CALCIUM GLUCONATE; CAMPHOR OIL; CETEARYL GLUCOSIDE; CETYL ALCOHOL; GLUCONOLACTONE; CANNABIS SATIVA FLOWERING TOP; ALOE VERA LEAF; GLYCERIN; LAVENDER OIL; OLIVE OIL; PEPPERMINT OIL; ROSEMARY OIL; SWEET MARJORAM OIL; METHYL SALICYLATE; POTASSIUM SORBATE; CARTHAMUS TINCTORIUS SEED OLEOSOMES; SODIUM BENZOATE; SODIUM CHLORIDE; SODIUM STEAROYL GLUTAMATE; SORBITAN OLIVATE; TOCOPHEROL; WATER; XANTHAN GUM

JOY SKIN & BODY Premium PAIN RELIEVING CREAM

Active ingredient

Menthol 4%

Purpose

External analgesic

Use

For the temporary relief of minor aches and pains of the muscles and joints associated with

• arthritis • simple backache • sprains • strains • bruises

Warnings

Flammable: Keep away from fire or flame

For external use only.

Do not use

• on wounds or damaged skin.

When using this product

• avoid contact with the eyes. If contact occurs, rinse with water to remove

• do not bandage tightly

Stop use and ask a doctor if

• condition worsens or if symptoms persist for more than 7 days or clear up and occur again within a few days

If pregnant or breast-feeding, ask a health professional before use.

Keep out of reach of children. If swallowed, get medical help or contact a Poison Control Center right away.

Directions

• adults and children 2 years of age and older: Apply to affected area not more than 3 to 4 times daily.

• children under 2 years of age: consult a doctor.

Other information

• protect this product from excessive heat and direct sun.

• store at room temperature.

Inactive ingredients

Calcium Gluconate, Camphor(Cinnamomum camphora) Oil (0.5%), Cetearyl Glucoside, Cetyl Alcohol, Glucono delta-lactone, Hemp (Cannabis sativa) Extract, Organic Aloe Vera Leaf Juice (0.02%), Organic Glycerin (3%), Organic Lavender(Lavandula angustifolia) Oil (0.1%), Organic Olive(Olea europaea) Oil (10%), Organic Peppermint(Mentha piperita) Oil (0.1%), Organic Rosemary(Rosmarinus officinalis) Oil (0.1%), Organic Sweet Marjoram(Origanum majorana) Oil (0.1%), Organic Wintergreen(Gaultheria procumbens) Oil (0.1%), Potassium Sorbate, Safflower (Carthamus tinctorius) Oleosomes Extract, Sodium Benzoate, Sodium Chloride, Sodium Stearoyl Glutamate, Sorbitan Olivate, Tocopherol, Water(Aqua), Xanthan Gum.

Questions? +1-833-569-7223

You may also report serious side effects to this phone number.

Mon - Fri: 9 AM to 5 PM

4% Cooling Menthol for Pain Relief

Cool Menthol

Includes Hemp Extract, Rosemary & Lavender Oil

BROAD SPECTRUM

NON GMO

0.0% THC

USA HEMP

PREMIUM GRADE

Joy's cooling Menthol Pain Relieving Cream combines premium ingredients with efficacious amounts of Menthol to reduce pain and alleviate muscle and joint aches.

This unique formula with Menthol also includes 400mg of CBD oil and a variety of other natural ingredients including, olive oil, rosemary oil, and lavender oils for soothing and powerful results.

OUR PROCESS

Each ingredient in this formula is meticulously sourced for both purity and quality.

LAB RESULTS

Every batch of our products is rigorously tested by an ISO-certified lab for heavy metals, pesticides, molds, CBD and THC.

Manufactured for
Joy Organics, LLC

5042 Technology Pkwy.
Suite 500,
Fort Collins, CO 80528

JoyOrganics.com

Scan QR code or visit JoyOrganics.com/labs to view the lab results.

Live your BEST LIFE